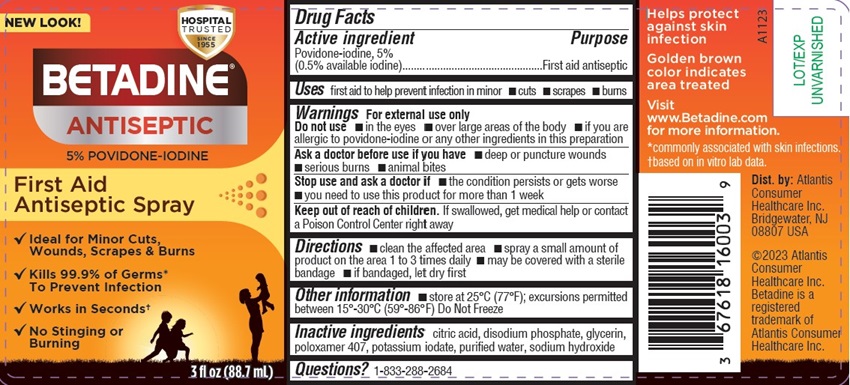 DRUG LABEL: Betadine
NDC: 67618-160 | Form: SPRAY
Manufacturer: Atlantis Consumer Healthcare, Inc.
Category: otc | Type: HUMAN OTC DRUG LABEL
Date: 20251224

ACTIVE INGREDIENTS: POVIDONE-IODINE 5 mg/1 mL
INACTIVE INGREDIENTS: CITRIC ACID MONOHYDRATE; SODIUM PHOSPHATE, DIBASIC, MONOHYDRATE; GLYCERIN; POLOXAMER 407; POTASSIUM IODATE; WATER; SODIUM HYDROXIDE

BETADINE® Spray
5% Povidone-iodine

Drug Facts

Active ingredients

Povidone-iodine, 5%(0.5% available iodine)

Purpose

First aid Antiseptic

Uses

First aidto help prevent infection in minor

- cuts
- scrapes
- burns

Warnings

For external use only

Do not use

- in the eyes
- over large areas of the body
- If you are allergic to povidone-iodine or any other ingredientsin this preparation

Ask a doctor before useif you have

- deep or puncture wounds
- serious burns
- animal bites

Stop use and ask a doctor if

- the condition persists or gets worse
- you need to use this product for more than 1 week

Keep out of reach of children. If swallowed, get medical help or contact a Poison Control Centerright away.

Directions

- clean the affected area
- spray a small amount of the product on the area 1 to 3 timesa daily
- may be covered with sterile bandage
- if bandaged, let dry first

Other information

store at25⁰C (77⁰F); excursions permitted between 15⁰-30⁰C (59⁰-86⁰F) Do NotFreeze

Inactive ingredients

citric acid, disodium phosphate, glycerin,poloxamer 407, potassium iodate, purified water, sodium hydroxide

Dist. by: Avrio Health L.P.Stamford, CT 06901-3431

PACKAGE LABEL

Betadine 3oz Spray
NDC: 67618-160-03